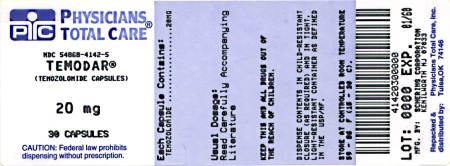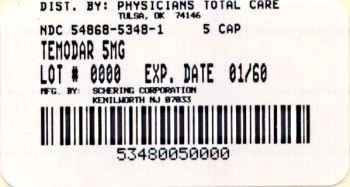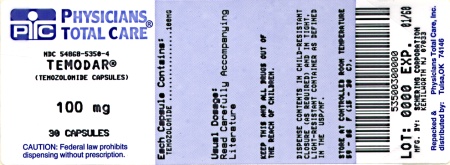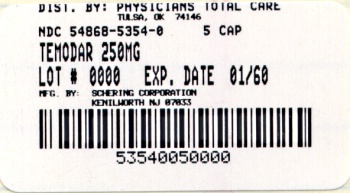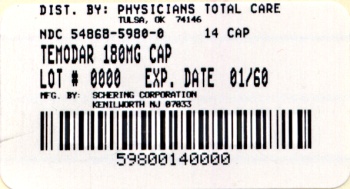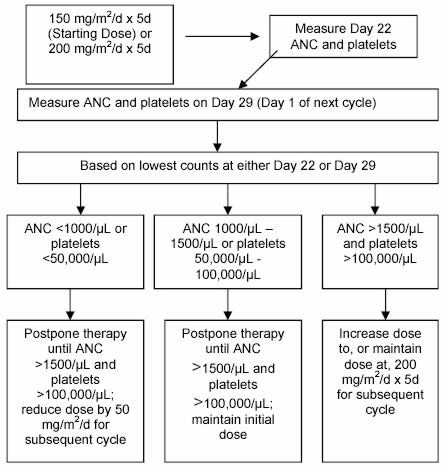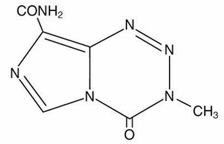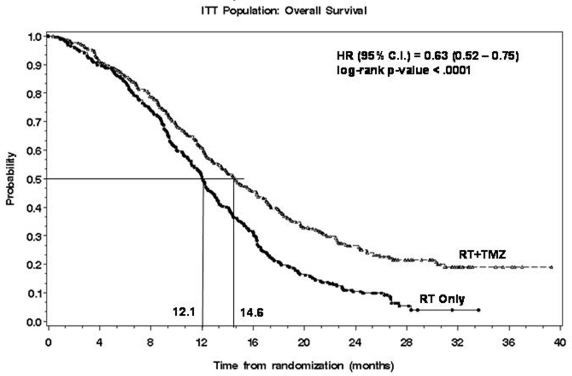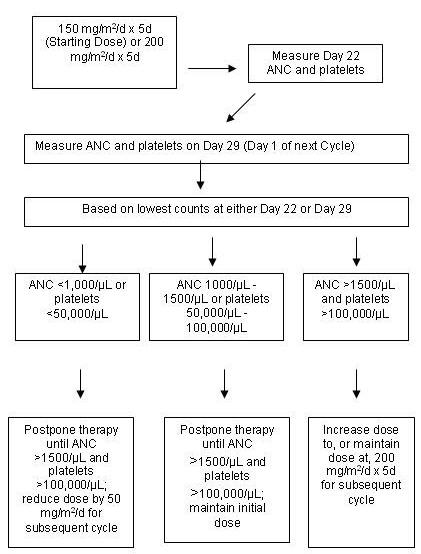 DRUG LABEL: TEMODAR
NDC: 54868-5348 | Form: CAPSULE
Manufacturer: Physicians Total Care, Inc.
Category: prescription | Type: HUMAN PRESCRIPTION DRUG LABEL
Date: 20110209

ACTIVE INGREDIENTS: Temozolomide 5 mg/1 1
INACTIVE INGREDIENTS: anhydrous lactose; silicon dioxide; sodium starch glycolate type A potato; tartaric acid; stearic acid; shellac; alcohol; isopropyl alcohol; butyl alcohol; propylene glycol; water; ammonia; potassium hydroxide; ferric oxide red; gelatin; titanium dioxide; ferric oxide yellow; sodium lauryl sulfate; FD&C Blue No. 2

HIGHLIGHTS OF PRESCRIBING INFORMATION

These highlights do not include all the information needed to use TEMODAR safely and effectively. See full prescribing information for TEMODAR.
TEMODAR (temozolomide) Capsules
TEMODAR (temozolomide) for Injection administered via intravenous infusion
Initial U.S. Approval: 1999

RECENT MAJOR CHANGES

Dosage and Administration, Preparation and Administration (2.2) [02/2011]

1 INDICATIONS AND USAGE

TEMODAR is an alkylating drug indicated for the treatment of adult patients with:

- Newly diagnosed glioblastoma multiforme (GBM) concomitantly with radiotherapy and then as maintenance treatment. (1.1)
- Refractory anaplastic astrocytoma patients who have experienced disease progression on a drug regimen containing nitrosourea and procarbazine. (1.2)

2 DOSAGE AND ADMINISTRATION

- Newly Diagnosed GBM: 75 mg/m^2 for 42 days concomitant with focal radiotherapy followed by initial maintenance dose of 150 mg/m^2 once daily for Days 1–5 of a 28-day cycle of TEMODAR for 6 cycles. (2.1)
- Refractory Anaplastic Astrocytoma: Initial dose 150 mg/m^2 once daily for 5 consecutive days per 28-day treatment cycle. (2.1)
- The recommended dose for TEMODAR as an intravenous infusion over 90 minutes is the same as the dose for the oral capsule formulation. Bioequivalence has been established only when TEMODAR for Injection was given over 90 minutes. (2.1, 12.3)

3 DOSAGE FORMS AND STRENGTHS

- 5-mg, 20-mg, 100-mg, 140-mg, 180-mg, and 250-mg capsules. (3)
- 100-mg powder for injection. (3)

4 CONTRAINDICATIONS

- Known hypersensitivity to any TEMODAR component or to dacarbazine (DTIC). (4.1)

5 WARNINGS AND PRECAUTIONS

- Myelosuppression - monitor Absolute Neutrophil Count (ANC) and platelet count prior to dosing and throughout treatment. Geriatric patients and women have a higher risk of developing myelosuppression. (5.1)
- Cases of myelodysplastic syndrome and secondary malignancies, including myeloid leukemia, have been observed. (5.2)
- Pneumocystis carinii pneumonia (PCP) – prophylaxis required for all patients receiving concomitant TEMODAR and radiotherapy for the 42-day regimen for the treatment of newly diagnosed glioblastoma multiforme. (5.3)
- All patients, particularly those receiving steroids, should be observed closely for the development of lymphopenia and PCP. (5.4)
- Complete blood counts should be obtained throughout the treatment course as specified. (5.4)
- Fetal harm can occur when administered to a pregnant woman. Women should be advised to avoid becoming pregnant when receiving TEMODAR. (5.5)
- As bioequivalence has been established only when given over 90 minutes, infusion over a shorter or longer period of time may result in suboptimal dosing; the possibility of an increase in infusion-related adverse reactions cannot be ruled out. (5.6)

6 ADVERSE REACTIONS

- The most common adverse reactions (≥10% incidence) are: alopecia, fatigue, nausea, vomiting, headache, constipation, anorexia, convulsions, rash, hemiparesis, diarrhea, asthenia, fever, dizziness, coordination abnormal, viral infection, amnesia, and insomnia. (6.1)
- The most common Grade 3 to 4 hematologic laboratory abnormalities (≥10% incidence) that have developed during treatment with temozolomide are: lymphopenia, thrombocytopenia, neutropenia, and leukopenia. (6.1)
- Allergic reactions have also been reported. (6)

To report SUSPECTED ADVERSE REACTIONS, contact Schering Corporation, a subsidiary of Merck & Co., Inc. at 1-800-526-4099 or FDA at 1-800-FDA-1088 or www.fda.gov/medwatch

7 DRUG INTERACTIONS

- Valproic acid: decreases oral clearance of temozolomide. (7.1)

8 USE IN SPECIFIC POPULATIONS

- Nursing mothers: Not recommended. (8.3)
- Pediatric use: No established use. (8.4)
- Hepatic/Renal Impairment: Caution should be exercised when TEMODAR is administered to patients with severe renal or hepatic impairment. (8.6, 8.7)

FULL PRESCRIBING INFORMATION

1 INDICATIONS AND USAGE

1.1 Newly Diagnosed Glioblastoma Multiforme

TEMODAR® (temozolomide) is indicated for the treatment of adult patients with newly diagnosed glioblastoma multiforme concomitantly with radiotherapy and then as maintenance treatment.

1.2 Refractory Anaplastic Astrocytoma

TEMODAR is indicated for the treatment of adult patients with refractory anaplastic astrocytoma, i.e., patients who have experienced disease progression on a drug regimen containing nitrosourea and procarbazine.

2 DOSAGE AND ADMINISTRATION

2.1 Recommended Dosing and Dose Modification Guidelines

The recommended dose for TEMODAR as an intravenous infusion over 90 minutes is the same as the dose for the oral capsule formulation. Bioequivalence has been established only when TEMODAR for Injection was given over 90 minutes [see Clinical Pharmacology (12.3)]. Dosage of TEMODAR must be adjusted according to nadir neutrophil and platelet counts in the previous cycle and the neutrophil and platelet counts at the time of initiating the next cycle. For TEMODAR dosage calculations based on body surface area (BSA) see Table 5. For suggested capsule combinations on a daily dose see Table 6.

Patients with Newly Diagnosed High Grade Glioma:

Concomitant Phase:

TEMODAR is administered at 75 mg/m^2 daily for 42 days concomitant with focal radiotherapy (60 Gy administered in 30 fractions) followed by maintenance TEMODAR for 6 cycles. Focal RT includes the tumor bed or resection site with a 2- to 3-cm margin. No dose reductions are recommended during the concomitant phase; however, dose interruptions or discontinuation may occur based on toxicity. The TEMODAR dose should be continued throughout the 42-day concomitant period up to 49 days if all of the following conditions are met: absolute neutrophil count ≥1.5 × 10^9 /L, platelet count ≥100 × 10^9/L, common toxicity criteria (CTC) nonhematological toxicity ≤Grade 1 (except for alopecia, nausea, and vomiting). During treatment a complete blood count should be obtained weekly. Temozolomide dosing should be interrupted or discontinued during concomitant phase according to the hematological and nonhematological toxicity criteria as noted in Table 1. PCP prophylaxis is required during the concomitant administration of TEMODAR and radiotherapy and should be continued in patients who develop lymphocytopenia until recovery from lymphocytopenia (CTC Grade ≤1).

TABLE 1: Temozolomide Dosing Interruption or Discontinuation During Concomitant Radiotherapy and Temozolomide
Toxicity | TMZ Interruption [Treatment with concomitant TMZ could be continued when all of the following conditions were met: absolute neutrophil count ≥1.5 × 10^9/L; platelet count ≥100 × 10^9/L; CTC nonhematological toxicity ≤Grade 1 (except for alopecia, nausea, vomiting).] | TMZ Discontinuation
Absolute Neutrophil Count | ≥0.5 and <1.5 × 10^9/L | <0.5 × 10^9/L
Platelet Count | ≥10 and <100 × 10^9/L | <10 × 10^9/L
CTC Nonhematological Toxicity (except for alopecia, nausea, vomiting) | CTC Grade 2 | CTC Grade 3 or 4
TMZ=temozolomide; CTC=Common Toxicity Criteria.

Maintenance Phase:

Cycle 1:

Four weeks after completing the TEMODAR+RT phase, TEMODAR is administered for an additional 6 cycles of maintenance treatment. Dosage in Cycle 1 (maintenance) is 150 mg/m^2 once daily for 5 days followed by 23 days without treatment.

Cycles 2–6:

At the start of Cycle 2, the dose can be escalated to 200 mg/m^2, if the CTC nonhematologic toxicity for Cycle 1 is Grade ≤2 (except for alopecia, nausea, and vomiting), absolute neutrophil count (ANC) is ≥1.5 × 10^9/L, and the platelet count is ≥100 × 10^9/L. The dose remains at 200 mg/m^2 per day for the first 5 days of each subsequent cycle except if toxicity occurs. If the dose was not escalated at Cycle 2, escalation should not be done in subsequent cycles.

Dose Reduction or Discontinuation During Maintenance:

Dose reductions during the maintenance phase should be applied according to Tables 2 and 3.

During treatment, a complete blood count should be obtained on Day 22 (21 days after the first dose of TEMODAR) or within 48 hours of that day, and weekly until the ANC is above 1.5 × 10^9/L (1500/µL) and the platelet count exceeds 100 × 10^9/L (100,000/µL). The next cycle of TEMODAR should not be started until the ANC and platelet count exceed these levels. Dose reductions during the next cycle should be based on the lowest blood counts and worst nonhematologic toxicity during the previous cycle. Dose reductions or discontinuations during the maintenance phase should be applied according to Tables 2 and 3.

TABLE 2: Temozolomide Dose Levels for Maintenance Treatment
Dose Level | Dose (mg/m^2/day) | Remarks
−1 | 100 | Reduction for prior toxicity
0 | 150 | Dose during Cycle 1
1 | 200 | Dose during Cycles 2–6 in absence of toxicity

TABLE 3: Temozolomide Dose Reduction or Discontinuation During Maintenance Treatment
Toxicity | Reduce TMZ by 1 Dose Level [TMZ dose levels are listed in Table 2.] | Discontinue TMZ
Absolute Neutrophil Count | <1.0 × 10^9/L | See footnote [TMZ is to be discontinued if dose reduction to <100 mg/m^2 is required or if the same Grade 3 nonhematological toxicity (except for alopecia, nausea, vomiting) recurs after dose reduction.]
Platelet Count | <50 × 10^9/L | See footnote
CTC Nonhematological Toxicity (except for alopecia, nausea, vomiting) | CTC Grade 3 | CTC Grade 4
TMZ=temozolomide; CTC=Common Toxicity Criteria.

Patients with Refractory Anaplastic Astrocytoma:

For adults the initial dose is 150 mg/m^2 once daily for 5 consecutive days per 28-day treatment cycle. For adult patients, if both the nadir and day of dosing (Day 29, Day 1 of next cycle) ANC are ≥1.5 × 10^9/L (1500/µL) and both the nadir and Day 29, Day 1 of next cycle platelet counts are ≥100 × 10^9/L (100,000/µL), the TEMODAR dose may be increased to 200 mg/m^2/day for 5 consecutive days per 28-day treatment cycle. During treatment, a complete blood count should be obtained on Day 22 (21 days after the first dose) or within 48 hours of that day, and weekly until the ANC is above 1.5 × 10^9/L (1500/µL) and the platelet count exceeds 100 × 10^9/L (100,000/µL). The next cycle of TEMODAR should not be started until the ANC and platelet count exceed these levels. If the ANC falls to <1.0 × 10^9/L (1000/µL) or the platelet count is <50 × 10^9/L (50,000/µL) during any cycle, the next cycle should be reduced by 50 mg/m^2, but not below 100 mg/m^2, the lowest recommended dose (see Table 4). TEMODAR therapy can be continued until disease progression. In the clinical trial, treatment could be continued for a maximum of 2 years, but the optimum duration of therapy is not known.

TABLE 4: Dosing Modification Table

TABLE 5: Daily Dose Calculations by Body Surface Area (BSA)
Total BSA (m^2) | 75 mg/m^2 (mg daily) | 150 mg/m^2 (mg daily) | 200 mg/m^2 (mg daily)
1.0 | 75 | 150 | 200
1.1 | 82.5 | 165 | 220
1.2 | 90 | 180 | 240
1.3 | 97.5 | 195 | 260
1.4 | 105 | 210 | 280
1.5 | 112.5 | 225 | 300
1.6 | 120 | 240 | 320
1.7 | 127.5 | 255 | 340
1.8 | 135 | 270 | 360
1.9 | 142.5 | 285 | 380
2.0 | 150 | 300 | 400
2.1 | 157.5 | 315 | 420
2.2 | 165 | 330 | 440
2.3 | 172.5 | 345 | 460
2.4 | 180 | 360 | 480
2.5 | 187.5 | 375 | 500

TABLE 6: Suggested Capsule Combinations Based on Daily Dose in Adults
Number of Daily Capsules by Strength (mg)
Total Daily Dose (mg) | 250 mg | 180 mg | 140 mg | 100 mg | 20 mg | 5 mg
75 | 0 | 0 | 0 | 0 | 3 | 3
82.5 | 0 | 0 | 0 | 0 | 4 | 0
90 | 0 | 0 | 0 | 0 | 4 | 2
97.5 | 0 | 0 | 0 | 1 | 0 | 0
105 | 0 | 0 | 0 | 1 | 0 | 1
112.5 | 0 | 0 | 0 | 1 | 0 | 2
120 | 0 | 0 | 0 | 1 | 1 | 0
127.5 | 0 | 0 | 0 | 1 | 1 | 1
135 | 0 | 0 | 0 | 1 | 1 | 3
142.5 | 0 | 0 | 1 | 0 | 0 | 0
150 | 0 | 0 | 1 | 0 | 0 | 2
157.5 | 0 | 0 | 1 | 0 | 1 | 0
165 | 0 | 0 | 1 | 0 | 1 | 1
172.5 | 0 | 0 | 1 | 0 | 1 | 2
180 | 0 | 1 | 0 | 0 | 0 | 0
187.5 | 0 | 1 | 0 | 0 | 0 | 1
195 | 0 | 1 | 0 | 0 | 0 | 3
200 | 0 | 1 | 0 | 0 | 1 | 0
210 | 0 | 0 | 0 | 2 | 0 | 2
220 | 0 | 0 | 0 | 2 | 1 | 0
225 | 0 | 0 | 0 | 2 | 1 | 1
240 | 0 | 0 | 1 | 1 | 0 | 0
255 | 1 | 0 | 0 | 0 | 0 | 1
260 | 1 | 0 | 0 | 0 | 0 | 2
270 | 1 | 0 | 0 | 0 | 1 | 0
280 | 0 | 0 | 2 | 0 | 0 | 0
285 | 0 | 0 | 2 | 0 | 0 | 1
300 | 0 | 0 | 0 | 3 | 0 | 0
315 | 0 | 0 | 0 | 3 | 0 | 3
320 | 0 | 1 | 1 | 0 | 0 | 0
330 | 0 | 1 | 1 | 0 | 0 | 2
340 | 0 | 1 | 1 | 0 | 1 | 0
345 | 0 | 1 | 1 | 0 | 1 | 1
360 | 0 | 2 | 0 | 0 | 0 | 0
375 | 0 | 2 | 0 | 0 | 0 | 3
380 | 0 | 1 | 0 | 2 | 0 | 0
400 | 0 | 0 | 0 | 4 | 0 | 0
420 | 0 | 0 | 3 | 0 | 0 | 0
440 | 0 | 0 | 3 | 0 | 1 | 0
460 | 0 | 2 | 0 | 1 | 0 | 0
480 | 0 | 1 | 0 | 3 | 0 | 0
500 | 2 | 0 | 0 | 0 | 0 | 0

2.2 Preparation and Administration

TEMODAR Capsules:

In clinical trials, TEMODAR was administered under both fasting and nonfasting conditions; however, absorption is affected by food [see Clinical Pharmacology (12)], and consistency of administration with respect to food is recommended. There are no dietary restrictions with TEMODAR. To reduce nausea and vomiting, TEMODAR should be taken on an empty stomach. Bedtime administration may be advised. Antiemetic therapy may be administered prior to and/or following administration of TEMODAR.

TEMODAR (temozolomide) Capsules should not be opened or chewed. They should be swallowed whole with a glass of water.

If capsules are accidentally opened or damaged, precautions should be taken to avoid inhalation or contact with the skin or mucous membranes [see How Supplied/Storage and Handling (16.1)].

TEMODAR for Injection:

Each vial of TEMODAR for Injection contains sterile and pyrogen-free temozolomide lyophilized powder. When reconstituted with 41 mL Sterile Water for Injection, the resulting solution will contain 2.5 mg/mL temozolomide. Bring the vial to room temperature prior to reconstitution with Sterile Water for Injection. The vials should be gently swirled and not shaken. Vials should be inspected, and any vial containing visible particulate matter should not be used. Do not further dilute the reconstituted solution. After reconstitution, store at room temperature (25°C [77°F]). Reconstituted product must be used within 14 hours, including infusion time.

Using aseptic technique, withdraw up to 40 mL from each vial to make up the total dose based on Table 5 above and transfer into an empty 250 mL infusion bag.^2 TEMODAR for Injection should be infused intravenously using a pump over a period of 90 minutes. TEMODAR for Injection should be administered only by intravenous infusion. Flush the lines before and after each TEMODAR infusion.

TEMODAR for Injection may be administered in the same intravenous line with 0.9% Sodium Chloride injection only.

Because no data are available on the compatibility of TEMODAR for Injection with other intravenous substances or additives, other medications should not be infused simultaneously through the same intravenous line.

3 DOSAGE FORMS AND STRENGTHS

- TEMODAR (temozolomide) Capsules for oral administration
  - 5-mg capsules have opaque white bodies with green caps. The capsule body is imprinted with two stripes, the dosage strength, and the Schering-Plough logo. The cap is imprinted with "TEMODAR."
  - 20-mg capsules have opaque white bodies with yellow caps. The capsule body is imprinted with two stripes, the dosage strength, and the Schering-Plough logo. The cap is imprinted with "TEMODAR."
  - 100-mg capsules have opaque white bodies with pink caps. The capsule body is imprinted with two stripes, the dosage strength, and the Schering-Plough logo. The cap is imprinted with "TEMODAR."
  - 140-mg capsules have opaque white bodies with blue caps. The capsule body is imprinted with two stripes, the dosage strength, and the Schering-Plough logo. The cap is imprinted with "TEMODAR."
  - 180-mg capsules have opaque white bodies with orange caps. The capsule body is imprinted with two stripes, the dosage strength, and the Schering-Plough logo. The cap is imprinted with "TEMODAR."
  - 250-mg capsules have opaque white bodies with white caps. The capsule body is imprinted with two stripes, the dosage strength, and the Schering-Plough logo. The cap is imprinted with "TEMODAR."
- TEMODAR (temozolomide) is available as 100-mg/vial powder for injection. The lyophilized powder is white to light tan/light pink.

4 CONTRAINDICATIONS

4.1 Hypersensitivity

TEMODAR (temozolomide) is contraindicated in patients who have a history of hypersensitivity reaction (such as urticaria, allergic reaction including anaphylaxis, toxic epidermal necrolysis, and Stevens-Johnson syndrome) to any of its components. TEMODAR is also contraindicated in patients who have a history of hypersensitivity to DTIC, since both drugs are metabolized to 5-(3-methyltriazen-1-yl)-imidazole-4-carboxamide (MTIC).

5 WARNINGS AND PRECAUTIONS

5.1 Myelosuppression

Patients treated with TEMODAR may experience myelosuppression, including prolonged pancytopenia, which may result in aplastic anemia, which in some cases has resulted in a fatal outcome. In some cases, exposure to concomitant medications associated with aplastic anemia, including carbamazepine, phenytoin, and sulfamethoxazole/trimethoprim, complicates assessment. Prior to dosing, patients must have an absolute neutrophil count (ANC) ≥1.5 × 10^9/L and a platelet count ≥100 × 10^9/L. A complete blood count should be obtained on Day 22 (21 days after the first dose) or within 48 hours of that day, and weekly until the ANC is above 1.5 × 10^9/L and platelet count exceeds 100 × 10^9/L. Geriatric patients and women have been shown in clinical trials to have a higher risk of developing myelosuppression.

5.2 Myelodysplastic Syndrome

Cases of myelodysplastic syndrome and secondary malignancies, including myeloid leukemia, have been observed.

5.3 Pneumocystis carinii Pneumonia

For treatment of newly diagnosed glioblastoma multiforme: Prophylaxis against Pneumocystis carinii pneumonia is required for all patients receiving concomitant TEMODAR and radiotherapy for the 42-day regimen.

There may be a higher occurrence of PCP when temozolomide is administered during a longer dosing regimen. However, all patients receiving temozolomide, particularly patients receiving steroids, should be observed closely for the development of PCP regardless of the regimen.

5.4 Laboratory Tests

For the concomitant treatment phase with RT, a complete blood count should be obtained prior to initiation of treatment and weekly during treatment.

For the 28-day treatment cycles, a complete blood count should be obtained prior to treatment on Day 1 and on Day 22 (21 days after the first dose) of each cycle. Blood counts should be performed weekly until recovery if the ANC falls below 1.5 × 10^9/L and the platelet count falls below 100 × 10^9/L [see Recommended Dosing and Dose Modification Guidelines (2.1)].

5.5 Use in Pregnancy

TEMODAR can cause fetal harm when administered to a pregnant woman. Administration of TEMODAR to rats and rabbits during organogenesis at 0.38 and 0.75 times the maximum recommended human dose (75 and 150 mg/m^2), respectively, caused numerous fetal malformations of the external organs, soft tissues, and skeleton in both species [see Use in Specific Populations (8.1)].

5.6 Infusion Time

As bioequivalence has been established only when TEMODAR for Injection was given over 90 minutes, infusion over a shorter or longer period of time may result in suboptimal dosing. Additionally, the possibility of an increase in infusion-related adverse reactions cannot be ruled out.

6 ADVERSE REACTIONS

6.1 Clinical Trials Experience

Because clinical trials are conducted under widely varying conditions, adverse reaction rates observed in the clinical trials of a drug cannot be directly compared to rates in the clinical trials of another drug and may not reflect the rates observed in practice.

Newly Diagnosed Glioblastoma Multiforme:

During the concomitant phase (TEMODAR+radiotherapy), adverse reactions including thrombocytopenia, nausea, vomiting, anorexia, and constipation were more frequent in the TEMODAR+RT arm. The incidence of other adverse reactions was comparable in the two arms. The most common adverse reactions across the cumulative TEMODAR experience were alopecia, nausea, vomiting, anorexia, headache, and constipation (see Table 7). Forty-nine percent (49%) of patients treated with TEMODAR reported one or more severe or life-threatening reactions, most commonly fatigue (13%), convulsions (6%), headache (5%), and thrombocytopenia (5%). Overall, the pattern of reactions during the maintenance phase was consistent with the known safety profile of TEMODAR.

TABLE 7: Number (%) of Patients with Adverse Reactions: All and Severe/Life Threatening (Incidence of 5% or Greater)
 | Concomitant Phase RT Alone (n=285) |  |  |  | Concomitant Phase RT+TMZ (n=288) [One patient who was randomized to RT only arm received RT+temozolomide.] |  |  |  | Maintenance Phase TMZ (n=224)
 | All |  | Grade ≥3 |  | All |  | Grade ≥3 |  | All |  | Grade ≥3
Subjects Reporting any Adverse Reaction | 258 | (91) | 74 | (26) | 266 | (92) | 80 | (28) | 206 | (92) | 82 | (37)
Body as a Whole - General Disorders
Anorexia | 25 | (9) | 1 | (<1) | 56 | (19) | 2 | (1) | 61 | (27) | 3 | (1)
Dizziness | 10 | (4) | 0 |  | 12 | (4) | 2 | (1) | 12 | (5) | 0
Fatigue | 139 | (49) | 15 | (5) | 156 | (54) | 19 | (7) | 137 | (61) | 20 | (9)
Headache | 49 | (17) | 11 | (4) | 56 | (19) | 5 | (2) | 51 | (23) | 9 | (4)
Weakness | 9 | (3) | 3 | (1) | 10 | (3) | 5 | (2) | 16 | (7) | 4 | (2)
Central and Peripheral Nervous System Disorders
Confusion | 12 | (4) | 6 | (2) | 11 | (4) | 4 | (1) | 12 | (5) | 4 | (2)
Convulsions | 20 | (7) | 9 | (3) | 17 | (6) | 10 | (3) | 25 | (11) | 7 | (3)
Memory Impairment | 12 | (4) | 1 | (<1) | 8 | (3) | 1 | (<1) | 16 | (7) | 2 | (1)
Disorders of the Eye
Vision Blurred | 25 | (9) | 4 | (1) | 26 | (9) | 2 | (1) | 17 | (8) | 0
Disorders of the Immune System
Allergic Reaction | 7 | (2) | 1 | (<1) | 13 | (5) | 0 |  | 6 | (3) | 0
Gastrointestinal System Disorders
Abdominal Pain | 2 | (1) | 0 |  | 7 | (2) | 1 | (<1) | 11 | (5) | 1 | (<1)
Constipation | 18 | (6) | 0 |  | 53 | (18) | 3 | (1) | 49 | (22) | 0
Diarrhea | 9 | (3) | 0 |  | 18 | (6) | 0 |  | 23 | (10) | 2 | (1)
Nausea | 45 | (16) | 1 | (<1) | 105 | (36) | 2 | (1) | 110 | (49) | 3 | (1)
Stomatitis | 14 | (5) | 1 | (<1) | 19 | (7) | 0 |  | 20 | (9) | 3 | (1)
Vomiting | 16 | (6) | 1 | (<1) | 57 | (20) | 1 | (<1) | 66 | (29) | 4 | (2)
Injury and Poisoning
Radiation Injury NOS | 11 | (4) | 1 | (<1) | 20 | (7) | 0 |  | 5 | (2) | 0
Musculoskeletal System Disorders
Arthralgia | 2 | (1) | 0 |  | 7 | (2) | 1 | (<1) | 14 | (6) | 0
Platelet, Bleeding and Clotting Disorders
Thrombocytopenia | 3 | (1) | 0 |  | 11 | (4) | 8 | (3) | 19 | (8) | 8 | (4)
Psychiatric Disorders
Insomnia | 9 | (3) | 1 | (<1) | 14 | (5) | 0 |  | 9 | (4) | 0
Respiratory System Disorders
Coughing | 3 | (1) | 0 |  | 15 | (5) | 2 | (1) | 19 | (8) | 1 | (<1)
Dyspnea | 9 | (3) | 4 | (1) | 11 | (4) | 5 | (2) | 12 | (5) | 1 | (<1)
Skin and Subcutaneous Tissue Disorders
Alopecia | 179 | (63) | 0 |  | 199 | (69) | 0 |  | 124 | (55) | 0
Dry Skin | 6 | (2) | 0 |  | 7 | (2) | 0 |  | 11 | (5) | 1 | (<1)
Erythema | 15 | (5) | 0 |  | 14 | (5) | 0 |  | 2 | (1) | 0
Pruritus | 4 | (1) | 0 |  | 11 | (4) | 0 |  | 11 | (5) | 0
Rash | 42 | (15) | 0 |  | 56 | (19) | 3 | (1) | 29 | (13) | 3 | (1)
Special Senses Other, Disorders
Taste Perversion | 6 | (2) | 0 |  | 18 | (6) | 0 |  | 11 | (5) | 0
RT+TMZ=radiotherapy plus temozolomide; NOS=not otherwise specified.
Note: Grade 5 (fatal) adverse reactions are included in the Grade ≥3 column.

Myelosuppression (neutropenia and thrombocytopenia), which is a known dose-limiting toxicity for most cytotoxic agents, including TEMODAR, was observed. When laboratory abnormalities and adverse reactions were combined, Grade 3 or Grade 4 neutrophil abnormalities including neutropenic reactions were observed in 8% of the patients, and Grade 3 or Grade 4 platelet abnormalities, including thrombocytopenic reactions, were observed in 14% of the patients treated with TEMODAR.

Refractory Anaplastic Astrocytoma:

Tables 8 and 9 show the incidence of adverse reactions in the 158 patients in the anaplastic astrocytoma study for whom data are available. In the absence of a control group, it is not clear in many cases whether these reactions should be attributed to temozolomide or the patients' underlying conditions, but nausea, vomiting, fatigue, and hematologic effects appear to be clearly drug-related. The most frequently occurring adverse reactions were nausea, vomiting, headache, and fatigue. The adverse reactions were usually NCI Common Toxicity Criteria (CTC) Grade 1 or 2 (mild to moderate in severity) and were self-limiting, with nausea and vomiting readily controlled with antiemetics. The incidence of severe nausea and vomiting (CTC Grade 3 or 4) was 10% and 6%, respectively. Myelosuppression (thrombocytopenia and neutropenia) was the dose-limiting adverse reaction. It usually occurred within the first few cycles of therapy and was not cumulative.

Myelosuppression occurred late in the treatment cycle and returned to normal, on average, within 14 days of nadir counts. The median nadirs occurred at 26 days for platelets (range: 21–40 days) and 28 days for neutrophils (range: 1–44 days). Only 14% (22/158) of patients had a neutrophil nadir and 20% (32/158) of patients had a platelet nadir, which may have delayed the start of the next cycle. Less than 10% of patients required hospitalization, blood transfusion, or discontinuation of therapy due to myelosuppression.

In clinical trial experience with 110 to 111 women and 169 to 174 men (depending on measurements), there were higher rates of Grade 4 neutropenia (ANC<500 cells/µL) and thrombocytopenia (<20,000 cells/µL) in women than men in the first cycle of therapy (12% vs. 5% and 9% vs. 3%, respectively).

In the entire safety database for which hematologic data exist (N=932), 7% (4/61) and 9.5% (6/63) of patients over age 70 experienced Grade 4 neutropenia or thrombocytopenia in the first cycle, respectively. For patients less than or equal to age 70, 7% (62/871) and 5.5% (48/879) experienced Grade 4 neutropenia or thrombocytopenia in the first cycle, respectively. Pancytopenia, leukopenia, and anemia have also been reported.

TABLE 8: Adverse Reactions in the Anaplastic Astrocytoma Trial in Adults (≥5%)
 | No. (%) of TEMODAR Patients (N=158)
 | All Reactions | Grade 3/4
Any Adverse Reaction | 153 (97) | 79 (50)
Body as a Whole
Headache | 65 (41) | 10 (6)
Fatigue | 54 (34) | 7 (4)
Asthenia | 20 (13) | 9 (6)
Fever | 21 (13) | 3 (2)
Back pain | 12 (8) | 4 (3)
Cardiovascular
Edema peripheral | 17 (11) | 1 (1)
Central and Peripheral Nervous System
Convulsions | 36 (23) | 8 (5)
Hemiparesis | 29 (18) | 10 (6)
Dizziness | 19 (12) | 1 (1)
Coordination abnormal | 17 (11) | 2 (1)
Amnesia | 16 (10) | 6 (4)
Insomnia | 16 (10) | 0
Paresthesia | 15 (9) | 1 (1)
Somnolence | 15 (9) | 5 (3)
Paresis | 13 (8) | 4 (3)
Urinary incontinence | 13 (8) | 3 (2)
Ataxia | 12 (8) | 3 (2)
Dysphasia | 11 (7) | 1 (1)
Convulsions local | 9 (6) | 0
Gait abnormal | 9 (6) | 1 (1)
Confusion | 8 (5) | 0
Endocrine
Adrenal hypercorticism | 13 (8) | 0
Gastrointestinal System
Nausea | 84 (53) | 16 (10)
Vomiting | 66 (42) | 10 (6)
Constipation | 52 (33) | 1 (1)
Diarrhea | 25 (16) | 3 (2)
Abdominal pain | 14 (9) | 2 (1)
Anorexia | 14 (9) | 1 (1)
Metabolic
Weight increase | 8 (5) | 0
Musculoskeletal System
Myalgia | 8 (5)
Psychiatric Disorders
Anxiety | 11 (7) | 1 (1)
Depression | 10 (6) | 0
Reproductive Disorders
Breast pain, female | 4 (6)
Resistance Mechanism Disorders
Infection viral | 17 (11) | 0
Respiratory System
Upper respiratory tract infection | 13 (8) | 0
Pharyngitis | 12 (8) | 0
Sinusitis | 10 (6) | 0
Coughing | 8 (5) | 0
Skin and Appendages
Rash | 13 (8) | 0
Pruritus | 12 (8) | 2 (1)
Urinary System
Urinary tract infection | 12 (8) | 0
Micturition increased frequency | 9 (6) | 0
Vision
Diplopia | 8 (5) | 0
Vision abnormal [Blurred vision; visual deficit; vision changes; vision troubles] | 8 (5)

TABLE 9: Adverse Hematologic Effects (Grade 3 to 4) in the Anaplastic Astrocytoma Trial in Adults
 | TEMODAR [Change from Grade 0 to 2 at baseline to Grade 3 or 4 during treatment.]
Hemoglobin | 7/158 (4%)
Lymphopenia | 83/152 (55%)
Neutrophils | 20/142 (14%)
Platelets | 29/156 (19%)
WBC | 18/158 (11%)

TEMODAR for injection delivers equivalent temozolomide dose and exposure to both temozolomide and 5-(3-methyltriazen-1-yl)-imidazole-4-carboxamide (MTIC) as the corresponding TEMODAR capsules. Adverse reactions probably related to treatment that were reported from the 2 studies with the intravenous formulation (n=35) that were not reported in studies using the TEMODAR capsules were: pain, irritation, pruritus, warmth, swelling, and erythema at infusion site as well as the following adverse reactions: petechiae and hematoma.

6.2 Postmarketing Experience

The following adverse reactions have been identified during postapproval use of TEMODAR. Because these reactions are reported voluntarily from a population of uncertain size, it is not always possible to reliably estimate their frequency or establish a causal relationship to the drug exposure.

TEMODAR Capsules: allergic reactions, including anaphylaxis, have been reported. Erythema multiforme has been reported, which resolved after discontinuation of TEMODAR and, in some cases, recurred upon rechallenge. Cases of toxic epidermal necrolysis and Stevens-Johnson syndrome have been reported.

There have been reported cases of hepatotoxicity, including elevations of liver enzymes, hyperbilirubinemia, cholestasis, and hepatitis.

Opportunistic infections including Pneumocystis carinii pneumonia (PCP) have also been reported. Cases of interstitial pneumonitis/pneumonitis, alveolitis, and pulmonary fibrosis have been reported. Prolonged pancytopenia, which may result in aplastic anemia, has been reported, and in some cases has resulted in a fatal outcome.

7 DRUG INTERACTIONS

7.1 Valproic Acid

Administration of valproic acid decreases oral clearance of temozolomide by about 5%. The clinical implication of this effect is not known [see Clinical Pharmacology (12.3)].

8 USE IN SPECIFIC POPULATIONS

8.1 Pregnancy

TERATOGENIC EFFECTS

Pregnancy Category D. See Warnings and Precautions section.

TEMODAR can cause fetal harm when administered to a pregnant woman. Five consecutive days of oral temozolomide administration of 0.38 and 0.75 times the highest recommended human dose (75 and 150 mg/m^2) in rats and rabbits, respectively, during the period of organogenesis caused numerous malformations of the external and internal soft tissues and skeleton in both species. Doses equivalent to 0.75 times the highest recommended human dose (150 mg/m^2) caused embryolethality in rats and rabbits as indicated by increased resorptions. There are no adequate and well-controlled studies in pregnant women. If this drug is used during pregnancy, or if the patient becomes pregnant while taking this drug, the patient should be apprised of the potential hazard to a fetus. Women of childbearing potential should be advised to avoid becoming pregnant during therapy with TEMODAR.

8.3 Nursing Mothers

It is not known whether this drug is excreted in human milk. Because many drugs are excreted in human milk and because of the potential for serious adverse reactions in nursing infants and tumorigenicity shown for temozolomide in animal studies, a decision should be made whether to discontinue nursing or to discontinue the drug, taking into account the importance of the drug to the mother from TEMODAR.

8.4 Pediatric Use

Safety and effectiveness in pediatric patients have not been established. TEMODAR Capsules have been studied in 2 open-label studies in pediatric patients (aged 3–18 years) at a dose of 160 to 200 mg/m^2 daily for 5 days every 28 days. In one trial, 29 patients with recurrent brain stem glioma and 34 patients with recurrent high grade astrocytoma were enrolled. All patients had recurrence following surgery and radiation therapy, while 31% also had disease progression following chemotherapy. In a second study conducted by the Children's Oncology Group (COG), 122 patients were enrolled, including patients with medulloblastoma/PNET (29), high grade astrocytoma (23), low grade astrocytoma (22), brain stem glioma (16), ependymoma (14), other CNS tumors (9), and non-CNS tumors (9). The TEMODAR toxicity profile in pediatric patients is similar to adults. Table 10 shows the adverse reactions in 122 children in the COG study.

TABLE 10: Adverse Reactions Reported in the Pediatric Cooperative Group Trial (≥10%)
 | No. (%) of TEMODAR Patients (N=122) [These various tumors included the following: PNET-medulloblastoma, glioblastoma, low grade astrocytoma, brain stem tumor, ependymoma, mixed glioma, oligodendroglioma, neuroblastoma, Ewing's sarcoma, pineoblastoma, alveolar soft part sarcoma, neurofibrosarcoma, optic glioma, and osteosarcoma.]
Body System/Organ Class | All Reactions | Grade 3/4
Adverse Reaction
Subjects Reporting an AE | 107 (88) | 69 (57)
Body as a Whole
Central and Peripheral Nervous System
Central cerebral CNS cortex | 22 (18) | 13 (11)
Gastrointestinal System
Nausea | 56 (46) | 5 (4)
Vomiting | 62 (51) | 4 (3)
Platelet, Bleeding and Clotting
Thrombocytopenia | 71 (58) | 31 (25)
Red Blood Cell Disorders
Decreased Hemoglobin | 62 (51) | 7 (6)
White Cell and RES Disorders
Decreased WBC | 71 (58) | 21 (17)
Lymphopenia | 73 (60) | 48 (39)
Neutropenia | 62 (51) | 24 (20)

8.5 Geriatric Use

Clinical studies of temozolomide did not include sufficient numbers of subjects aged 65 and over to determine whether they responded differently from younger subjects. Other reported clinical experience has not identified differences in responses between the elderly and younger patients. In general, dose selection for an elderly patient should be cautious, reflecting the greater frequency of decreased hepatic, renal, or cardiac function, and of concomitant disease or other drug therapy.

In the anaplastic astrocytoma study population, patients 70 years of age or older had a higher incidence of Grade 4 neutropenia and Grade 4 thrombocytopenia (2/8; 25%, P=0.31 and 2/10; 20%, P=0.09, respectively) in the first cycle of therapy than patients under 70 years of age [see Warnings and Precautions (5) and Adverse Reactions (6)].

In newly diagnosed patients with glioblastoma multiforme, the adverse reaction profile was similar in younger patients (<65 years) vs. older (≥65 years).

8.6 Renal Impairment

Caution should be exercised when TEMODAR is administered to patients with severe renal impairment [see Clinical Pharmacology (12.3)].

8.7 Hepatic Impairment

Caution should be exercised when TEMODAR is administered to patients with severe hepatic impairment [see Clinical Pharmacology (12.3)].

10 OVERDOSAGE

Doses of 500, 750, 1000, and 1250 mg/m^2 (total dose per cycle over 5 days) have been evaluated clinically in patients. Dose-limiting toxicity was hematologic and was reported with any dose but is expected to be more severe at higher doses. An overdose of 2000 mg per day for 5 days was taken by one patient and the adverse reactions reported were pancytopenia, pyrexia, multi-organ failure, and death. There are reports of patients who have taken more than 5 days of treatment (up to 64 days), with adverse reactions reported including bone marrow suppression, which in some cases was severe and prolonged, and infections and resulted in death. In the event of an overdose, hematologic evaluation is needed. Supportive measures should be provided as necessary.

11 DESCRIPTION

TEMODAR contains temozolomide, an imidazotetrazine derivative. The chemical name of temozolomide is 3,4-dihydro-3-methyl-4-oxoimidazo[5,1-d]-as-tetrazine-8-carboxamide. The structural formula is:

The material is a white to light tan/light pink powder with a molecular formula of C6H6N6O2 and a molecular weight of 194.15. The molecule is stable at acidic pH (<5) and labile at pH >7; hence TEMODAR can be administered orally and intravenously. The prodrug, temozolomide, is rapidly hydrolyzed to the active 5-(3-methyltriazen-1-yl) imidazole-4-carboxamide (MTIC) at neutral and alkaline pH values, with hydrolysis taking place even faster at alkaline pH.

TEMODAR Capsules:

Each capsule for oral use contains either 5 mg, 20 mg, 100 mg, 140 mg, 180 mg, or 250 mg of temozolomide.

The inactive ingredients for TEMODAR Capsules are as follows:

TEMODAR 5 mg: lactose anhydrous (132.8 mg), colloidal silicon dioxide (0.2 mg), sodium starch glycolate (7.5 mg), tartaric acid (1.5 mg), and stearic acid (3 mg).
TEMODAR 20 mg: lactose anhydrous (182.2 mg), colloidal silicon dioxide (0.2 mg), sodium starch glycolate (11 mg), tartaric acid (2.2 mg), and stearic acid (4.4 mg).
TEMODAR 100 mg: lactose anhydrous (175.7 mg), colloidal silicon dioxide (0.3 mg), sodium starch glycolate (15 mg), tartaric acid (3 mg), and stearic acid (6 mg).
TEMODAR 140 mg: lactose anhydrous (246 mg), colloidal silicon dioxide (0.4 mg), sodium starch glycolate (21 mg), tartaric acid (4.2 mg), and stearic acid (8.4 mg).
TEMODAR 180 mg: lactose anhydrous (316.3 mg), colloidal silicon dioxide (0.5 mg), sodium starch glycolate (27 mg), tartaric acid (5.4 mg), and stearic acid (10.8 mg).
TEMODAR 250 mg: lactose anhydrous (154.3 mg), colloidal silicon dioxide (0.7 mg), sodium starch glycolate (22.5 mg), tartaric acid (9 mg), and stearic acid (13.5 mg).

The body of the capsules are made of gelatin, and are opaque white. The cap is also made of gelatin, and the colors vary based on the dosage strength. The capsule body and cap are imprinted with pharmaceutical branding ink, which contains shellac, dehydrated alcohol, isopropyl alcohol, butyl alcohol, propylene glycol, purified water, strong ammonia solution, potassium hydroxide, and ferric oxide.

TEMODAR 5 mg: The green cap contains gelatin, titanium dioxide, iron oxide yellow, sodium lauryl sulfate, and FD&C Blue #2.
TEMODAR 20 mg: The yellow cap contains gelatin, sodium lauryl sulfate, and iron oxide yellow.
TEMODAR 100 mg: The pink cap contains gelatin, titanium dioxide, sodium lauryl sulfate, and iron oxide red.
TEMODAR 140 mg: The blue cap contains gelatin, sodium lauryl sulfate, and FD&C Blue #2.
TEMODAR 180 mg: The orange cap contains gelatin, iron oxide red, iron oxide yellow, titanium dioxide, and sodium lauryl sulfate.
TEMODAR 250 mg: The white cap contains gelatin, titanium dioxide, and sodium lauryl sulfate.

TEMODAR for Injection:

Each vial contains 100 mg of sterile and pyrogen-free temozolomide lyophilized powder for intravenous injection. The inactive ingredients are: mannitol (600 mg), L-threonine (160 mg), polysorbate 80 (120 mg), sodium citrate dihydrate (235 mg), and hydrochloric acid (160 mg).

12 CLINICAL PHARMACOLOGY

12.1 Mechanism of Action

Temozolomide is not directly active but undergoes rapid nonenzymatic conversion at physiologic pH to the reactive compound 5-(3-methyltriazen-1-yl)-imidazole-4-carboxamide (MTIC). The cytotoxicity of MTIC is thought to be primarily due to alkylation of DNA. Alkylation (methylation) occurs mainly at the O^6 and N^7 positions of guanine.

12.3 Pharmacokinetics

Absorption:

Temozolomide is rapidly and completely absorbed after oral administration with a peak plasma concentration (Cmax) achieved in a median Tmax of 1 hour. Food reduces the rate and extent of temozolomide absorption. Mean peak plasma concentration and AUC decreased by 32% and 9%, respectively, and median Tmax increased by 2-fold (from 1–2.25 hours) when temozolomide was administered after a modified high-fat breakfast.

A pharmacokinetic study comparing oral and intravenous temozolomide in 19 patients with primary CNS malignancies showed that 150 mg/m^2 TEMODAR for injection administered over 90 minutes is bioequivalent to 150 mg/m^2 TEMODAR oral capsules with respect to both Cmax and AUC of temozolomide and MTIC. Following a single 90-minute intravenous infusion of 150 mg/m^2, the geometric mean Cmax values for temozolomide and MTIC were 7.3 mcg/mL and 276 ng/mL, respectively. Following a single oral dose of 150 mg/m^2, the geometric mean Cmax values for temozolomide and MTIC were 7.5 mcg/mL and 282 ng/mL, respectively. Following a single 90-minute intravenous infusion of 150 mg/m^2, the geometric mean AUC values for temozolomide and MTIC were 24.6 mcg∙hr/mL and 891 ng∙hr/mL, respectively. Following a single oral dose of 150 mg/m^2, the geometric mean AUC values for temozolomide and MTIC were 23.4 mcg∙hr/mL and 864 ng∙hr/mL, respectively.

Distribution:

Temozolomide has a mean apparent volume of distribution of 0.4 L/kg (%CV=13%). It is weakly bound to human plasma proteins; the mean percent bound of drug-related total radioactivity is 15%.

Metabolism and Elimination:

Temozolomide is spontaneously hydrolyzed at physiologic pH to the active species, MTIC and to temozolomide acid metabolite. MTIC is further hydrolyzed to 5-amino-imidazole-4-carboxamide (AIC), which is known to be an intermediate in purine and nucleic acid biosynthesis, and to methylhydrazine, which is believed to be the active alkylating species. Cytochrome P450 enzymes play only a minor role in the metabolism of temozolomide and MTIC. Relative to the AUC of temozolomide, the exposure to MTIC and AIC is 2.4% and 23%, respectively.

Excretion:

About 38% of the administered temozolomide total radioactive dose is recovered over 7 days: 37.7% in urine and 0.8% in feces. The majority of the recovery of radioactivity in urine is unchanged temozolomide (5.6%), AIC (12%), temozolomide acid metabolite (2.3%), and unidentified polar metabolite(s) (17%). Overall clearance of temozolomide is about 5.5 L/hr/m^2. Temozolomide is rapidly eliminated, with a mean elimination half-life of 1.8 hours, and exhibits linear kinetics over the therapeutic dosing range of 75 to 250 mg/m^2/day.

Effect of Age:

A population pharmacokinetic analysis indicated that age (range: 19–78 years) has no influence on the pharmacokinetics of temozolomide.

Effect of Gender:

A population pharmacokinetic analysis indicated that women have an approximately 5% lower clearance (adjusted for body surface area) for temozolomide than men.

Effect of Race:

The effect of race on the pharmacokinetics of temozolomide has not been studied.

Tobacco Use:

A population pharmacokinetic analysis indicated that the oral clearance of temozolomide is similar in smokers and nonsmokers.

Effect of Renal Impairment:

A population pharmacokinetic analysis indicated that creatinine clearance over the range of 36 to 130 mL/min/m^2 has no effect on the clearance of temozolomide after oral administration. The pharmacokinetics of temozolomide have not been studied in patients with severely impaired renal function (CLcr <36 mL/min/m^2). Caution should be exercised when TEMODAR is administered to patients with severe renal impairment [see Use in Special Populations (8.6)]. TEMODAR has not been studied in patients on dialysis.

Effect of Hepatic Impairment:

A study showed that the pharmacokinetics of temozolomide in patients with mild-to-moderate hepatic impairment (Child-Pugh Class I – II) were similar to those observed in patients with normal hepatic function. Caution should be exercised when temozolomide is administered to patients with severe hepatic impairment [see Use in Special Populations (8.7)].

Effect of Other Drugs on Temozolomide Pharmacokinetics:

In a multiple-dose study, administration of TEMODAR Capsules with ranitidine did not change the Cmax or AUC values for temozolomide or MTIC.

A population analysis indicated that administration of valproic acid decreases the clearance of temozolomide by about 5% [see Drug Interactions (7)].

A population analysis did not demonstrate any influence of coadministered dexamethasone, prochlorperazine, phenytoin, carbamazepine, ondansetron, H2-receptor antagonists, or phenobarbital on the clearance of orally administered temozolomide.

13 NONCLINICAL TOXICOLOGY

13.1 Carcinogenesis, Mutagenesis, Impairment of Fertility

Temozolomide is carcinogenic in rats at doses less than the maximum recommended human dose. Temozolomide induced mammary carcinomas in both males and females at doses 0.13 to 0.63 times the maximum human dose (25–125 mg/m^2) when administered orally on 5 consecutive days every 28 days for 6 cycles. Temozolomide also induced fibrosarcomas of the heart, eye, seminal vesicles, salivary glands, abdominal cavity, uterus, and prostate, carcinomas of the seminal vesicles, schwannomas of the heart, optic nerve, and harderian gland, and adenomas of the skin, lung, pituitary, and thyroid at doses 0.5 times the maximum daily dose. Mammary tumors were also induced following 3 cycles of temozolomide at the maximum recommended daily dose.

Temozolomide is a mutagen and a clastogen. In a reverse bacterial mutagenesis assay (Ames assay), temozolomide increased revertant frequency in the absence and presence of metabolic activation. Temozolomide was clastogenic in human lymphocytes in the presence and absence of metabolic activation.

Temozolomide impairs male fertility. Temozolomide caused syncytial cells/immature sperm formation at 0.25 and 0.63 times the maximum recommended human dose (50 and 125 mg/m^2) in rats and dogs, respectively, and testicular atrophy in dogs at 0.63 times the maximum recommended human dose (125 mg/m^2).

13.2 Animal Toxicology and/or Pharmacology

Toxicology studies in rats and dogs identified a low incidence of hemorrhage, degeneration, and necrosis of the retina at temozolomide doses equal to or greater than 0.63 times the maximum recommended human dose (125 mg/m^2). These changes were most commonly seen at doses where mortality was observed.

14 CLINICAL STUDIES

14.1 Newly Diagnosed Glioblastoma Multiforme

Five hundred and seventy-three patients were randomized to receive either TEMODAR (TMZ)+Radiotherapy (RT) (n=287) or RT alone (n=286). Patients in the TEMODAR+RT arm received concomitant TEMODAR (75 mg/m^2) once daily, starting the first day of RT until the last day of RT, for 42 days (with a maximum of 49 days). This was followed by 6 cycles of TEMODAR alone (150 or 200 mg/m^2) on Days 1 to 5 of every 28-day cycle, starting 4 weeks after the end of RT. Patients in the control arm received RT only. In both arms, focal radiation therapy was delivered as 60 Gy/30 fractions. Focal RT includes the tumor bed or resection site with a 2- to 3-cm margin. Pneumocystis carinii pneumonia (PCP) prophylaxis was required during the TMZ + RT, regardless of lymphocyte count, and was to continue until recovery of lymphocyte count to less than or equal to Grade 1.

At the time of disease progression, TEMODAR was administered as salvage therapy in 161 patients of the 282 (57%) in the RT alone arm, and 62 patients of the 277 (22%) in the TEMODAR+RT arm.

The addition of concomitant and maintenance TEMODAR to radiotherapy in the treatment of patients with newly diagnosed GBM showed a statistically significant improvement in overall survival compared to radiotherapy alone (Figure 1). The hazard ratio (HR) for overall survival was 0.63 (95% CI for HR=0.52-0.75) with a log-rank P<0.0001 in favor of the TEMODAR arm. The median survival was increased by 2.5 months in the TEMODAR arm.

FIGURE 1: Kaplan-Meier Curves for Overall Survival (ITT Population)

14.2 Refractory Anaplastic Astrocytoma

A single-arm, multicenter study was conducted in 162 patients who had anaplastic astrocytoma at first relapse and who had a baseline Karnofsky performance status of 70 or greater. Patients had previously received radiation therapy and may also have previously received a nitrosourea with or without other chemotherapy. Fifty-four patients had disease progression on prior therapy with both a nitrosourea and procarbazine, and their malignancy was considered refractory to chemotherapy (refractory anaplastic astrocytoma population). Median age of this subgroup of 54 patients was 42 years (19–76). Sixty-five percent were male. Seventy-two percent of patients had a KPS of >80. Sixty-three percent of patients had surgery other than a biopsy at the time of initial diagnosis. Of those patients undergoing resection, 73% underwent a subtotal resection and 27% underwent a gross total resection. Eighteen percent of patients had surgery at the time of first relapse. The median time from initial diagnosis to first relapse was 13.8 months (4.2–75.4).

TEMODAR Capsules were given for the first 5 consecutive days of a 28-day cycle at a starting dose of 150 mg/m^2/day. If the nadir and day of dosing (Day 29, Day 1 of next cycle) absolute neutrophil count was ≥1.5 × 10^9/L (1500/µL) and the nadir and Day 29, Day 1 of next cycle platelet count was ≥100 × 10^9/L (100,000/µL), the TEMODAR dose was increased to 200 mg/m^2/day for the first 5 consecutive days of a 28-day cycle.

In the refractory anaplastic astrocytoma population, the overall tumor response rate (CR + PR) was 22% (12/54 patients) and the complete response rate was 9% (5/54 patients). The median duration of all responses was 50 weeks (range: 16–114 weeks) and the median duration of complete responses was 64 weeks (range:52–114 weeks). In this population, progression-free survival at 6 months was 45% (95% CI: 31%–58%) and progression-free survival at 12 months was 29% (95% CI: 16%–42%). Median progression-free survival was 4.4 months. Overall survival at 6 months was 74% (95% CI: 62%–86%) and 12-month overall survival was 65% (95% CI: 52%–78%). Median overall survival was 15.9 months.

15 REFERENCES

1. OSHA Technical Manual, TED 1-0.15A, Section VI: Chapter 2. Controlling Occupational Exposure to Hazardous Drugs. OSHA, 1999.
2. American Society of Health-System Pharmacists. ASHP guidelines on handling hazardous drugs. Am J Health-Syst Pharm. 2006; 63:1172–1193.
3. NIOSH Alert: Preventing occupational exposures to antineoplastic and other hazardous drugs in healthcare settings. 2004. U.S. Department of Health and Human Services, Public Health Service, Centers for Disease Control and Prevention, National Institute for Occupational Safety and Health, DHHS (NIOSH) Publication No. 2004-165.[3]
4. Polovich, M., White, J. M., & Kelleher, L.O. (eds.) 2005. Chemotherapy and biotherapy guidelines and recommendations for practice (2nd. ed.) Pittsburgh, PA: Oncology.

16 HOW SUPPLIED/STORAGE AND HANDLING

16.1 Safe Handling and Disposal

Care should be exercised in the handling and preparation of TEMODAR. Vials and capsules should not be opened. If vials or capsules are accidentally opened or damaged, rigorous precautions should be taken with the contents to avoid inhalation or contact with the skin or mucous membranes. The use of gloves and safety glasses is recommended to avoid exposure in case of breakage of the vial or capsules. Procedures for proper handling and disposal of anticancer drugs should be considered^1–4. Several guidelines on this subject have been published.

16.2 How Supplied

TEMODAR Capsules:

TEMODAR (temozolomide) Capsules are supplied in amber glass bottles with child-resistant polypropylene caps containing the following capsule strengths:

TEMODAR Capsules 5 mg: have opaque white bodies with green caps. The capsule body is imprinted with two stripes, the dosage strength, and the Schering-Plough logo. The cap is imprinted with "TEMODAR".
They are supplied as follows:
5-count - NDC 54868-5348-1

TEMODAR Capsules 20 mg: have opaque white bodies with yellow caps. The capsule body is imprinted with two stripes, the dosage strength, and the Schering-Plough logo. The cap is imprinted with "TEMODAR".
They are supplied as follows:
5-count - NDC 54868-4142-0
10-count - NDC 54868-4142-2
20-count - NDC 54868-4142-6
30-count - NDC 54868-4142-5
40-count - NDC 54868-4142-4
60-count - NDC 54868-4142-3

TEMODAR Capsules 100 mg: have opaque white bodies with pink caps. The capsule body is imprinted with two stripes, the dosage strength, and the Schering-Plough logo. The cap is imprinted with "TEMODAR".
They are supplied as follows:
5-count - NDC 54868-5350-2
10-count - NDC 54868-5350-3
15-count - NDC 54868-5350-0
30-count - NDC 54868-5350-4

TEMODAR Capsules 180 mg: have opaque white bodies with orange caps. The capsule body is imprinted with two stripes, the dosage strength, and the Schering-Plough logo. The cap is imprinted with "TEMODAR".
They are supplied as follows:
14-count - NDC 54868-5980-0

TEMODAR Capsules 250 mg: have opaque white bodies with white caps. The capsule body is imprinted with two stripes, the dosage strength, and the Schering-Plough logo. The cap is imprinted with "TEMODAR".
They are supplied as follows:
5-count - NDC 54868-5354-0

16.3 Storage

Store TEMODAR Capsules at 25°C (77°F); excursions permitted to 15°–30°C (59°–86°F)

[see USP Controlled Room Temperature].

Store TEMODAR for Injection refrigerated at 2°–8°C (36°–46°F). After reconstitution, store reconstituted product at room temperature (25°C [77°F]). Reconstituted product must be used within 14 hours, including infusion time.

17 PATIENT COUNSELING INFORMATION

17.1 Information for the Patient

Physicians should discuss the following with their patients:

- Nausea and vomiting are the most frequently occurring adverse reactions. Nausea and vomiting are usually either self-limiting or readily controlled with standard antiemetic therapy.
- Capsules should not be opened. If capsules are accidentally opened or damaged, rigorous precautions should be taken with the capsule contents to avoid inhalation or contact with the skin or mucous membranes.
- The medication should be kept away from children and pets.

TEMODAR Capsules
Manufactured by: Schering Corporation, a subsidiary of {corporate logo}MERCK & CO., INC., Whitehouse Station, NJ 08889, USA

TEMODAR for Injection
Manufactured by: Baxter Oncology GmbH, Halle/Westfalen, Germany
Distributed by: Schering Corporation, a subsidiary of {corporate logo}MERCK & CO., INC., Whitehouse Station, NJ 08889, USA

Copyright© 1999, 2008 Schering Corporation, a subsidiary of Merck & Co., Inc. All rights reserved.

TEMODAR Capsules: U.S. Patent No. 5,260,291
TEMODAR for Injection: US Patent Nos. 5,260,291; 6,987,108; 7,786,118

31850940T
Rev 2/11

Relabeling and Repackaging by:
Physicians Total Care, Inc.
Tulsa, OK 74146

PATIENT INFORMATION

Tear patient package insert at perforation and give to patient.

Patient Package Insert
TEMODAR® (tĕm-ō-dăr)
(temozolomide)
Capsules
TEMODAR® (tĕm-ō-dăr)
for Injection

What is the most important information I should know about TEMODAR?

- TEMODAR may cause birth defects. Male and female patients who take TEMODAR should use effective birth control. Female patients and female partners of male patients should avoid becoming pregnant while taking TEMODAR.

See the section "What are the possible side effects of TEMODAR?" for more information about side effects.

What is TEMODAR?

TEMODAR (temozolomide) is a prescription medicine used to treat adults with certain brain cancer tumors. TEMODAR blocks cell growth, especially cells that grow fast, such as cancer cells. TEMODAR may decrease the size of certain brain tumors in some patients.

It is not known if TEMODAR is safe and effective in children.

Who should not take TEMODAR?

Do not take TEMODAR if you:

- have had an allergic reaction to DTIC (dacarbazine), another cancer medicine.
- have had a red itchy rash, or a severe allergic reaction, such as trouble breathing, swelling of the face, throat, or tongue, or severe skin reaction to TEMODAR or any of the ingredients in TEMODAR. If you are not sure, ask your doctor. See the end of the leaflet for a list of ingredients in TEMODAR.

What should I tell my doctor before taking TEMODAR?

Tell your doctor about all your medical conditions, including if you:

- are allergic to DTIC (dacarbazine) or have had a severe allergic reaction to TEMODAR. See "Who should not take TEMODAR?"
- have kidney problems
- have liver problems
- are pregnant. See "What is the most important information I should know about TEMODAR?"
- are breast-feeding. It is not known whether TEMODAR passes into breast milk. You and your doctor should decide if you will breast-feed or take TEMODAR. You should not do both without talking with your doctor.

Tell your doctor about all the medicines you take, including prescription and non-prescription medicines, vitamins, and herbal supplements. Especially tell your doctor if you take a medicine that contains valproic acid (Stavzor®, Depakene®).

Know the medicines you take. Keep a list of them and show it to your doctor and pharmacist when you get a new medicine.

How should I take TEMODAR?

Temodar may be taken by mouth as a capsule at home, or you may receive TEMODAR by injection into a vein (intravenous). Your doctor will decide the best way for you to take TEMODAR.

There are two common dosing schedules for taking TEMODAR.

- Some people take TEMODAR for 42 days in a row (possibly 49 days depending on side effects) with radiation treatment. This is one cycle of treatment. After this, you may have "maintenance" treatment. Your doctor may prescribe 6 more cycles of TEMODAR. For each of these cycles, you take TEMODAR one time each day for 5 days in a row and then you stop taking it for the next 23 days. This is a 28-day maintenance treatment cycle.
- Another way to take TEMODAR is to take it one time each day for 5 days in a row only, and then you stop taking it for the next 23 days. This is one cycle of treatment (28 days). Your doctor will watch your progress on TEMODAR and decide how long you should take it. You might take TEMODAR until your tumor gets worse or for possibly up to 2 years.
- Your dose is based on your height and weight, and the number of treatment cycles will depend on how you respond to and tolerate this treatment.
- Your doctor may modify your schedule based on how you tolerate the treatment.
- If your doctor prescribes a treatment regimen that is different from the information in this leaflet, make sure you follow the specific instructions given to you by your doctor.

TEMODAR Capsules:

- Take TEMODAR Capsules exactly as prescribed.
- TEMODAR Capsules come in different strengths. Each strength has a different color cap. Your doctor may prescribe more than one strength of TEMODAR Capsules for you, so it is important that you understand how to take your medicine the right way. Be sure that you understand exactly how many capsules you need to take on each day of your treatment, and what strengths to take. This may be different whenever you start a new cycle.
- Talk to your doctor before you take your dose if you are not sure how much to take. This will help to prevent taking too much TEMODAR and decrease your chances of getting serious side effects.
- Take each day's dose of TEMODAR Capsules at one time, with a full glass of water.
- Swallow TEMODAR Capsules whole. Do not chew, open, or split the capsules.
- If TEMODAR capsules are accidentally opened or damaged, be careful not to breathe in (inhale) the powder from the capsules or get the powder on your skin or mucous membranes (for example, in your nose or mouth). If contact with any of these areas happens, flush the area with water.
- If you vomit TEMODAR Capsules, do not take any more capsules. Wait and take your next planned dose.
- The medicine is used best by your body if you take it at the same time every day in relation to a meal.
- To lessen nausea, try to take TEMODAR on an empty stomach or at bedtime. Your doctor may prescribe medicine to prevent or treat nausea, or other medicines to lessen side effects with TEMODAR.
- See your doctor regularly to check your progress. Your doctor will check you for side effects that you might not notice.
- If you miss a dose of TEMODAR, talk with your doctor for instructions about when to take your next dose of TEMODAR.
- Call your doctor right away if you take more than the prescribed amount of TEMODAR. It is important that you do not take more than the amount of TEMODAR prescribed for you.

TEMODAR for Injection:

- You will receive TEMODAR as an infusion directly into your vein. Your treatment will take about 90 minutes.
- Your doctor may prescribe medicine to prevent or treat nausea, or other medicines to relieve side effects with TEMODAR.

What should I avoid while taking TEMODAR?

- Female patients and female partners of male patients should avoid becoming pregnant while taking TEMODAR. See "What is the most important information I should know about TEMODAR?"

What are the possible side effects of TEMODAR?

TEMODAR can cause serious side effects.

- See "What is the most important information I should know about TEMODAR?"
- Decreased blood cells. TEMODAR affects cells that grow rapidly, including bone marrow cells. This can cause you to have a decrease in blood cells. Your doctor can monitor your blood for these effects.
  - White blood cells are needed to fight infections. Neutrophils are a type of white blood cell that help prevent bacterial infections. Decreased neutrophils can lead to serious infections that can lead to death. Other white blood cells called lymphocytes may also be decreased.
  - Platelets are blood cells needed for normal blood clotting. Low platelet counts can lead to bleeding. Tell your doctor about any unusual bruising or bleeding.

Your doctor will check your blood regularly while you are taking TEMODAR to see if these side effects are happening. Your doctor may need to change the dose of TEMODAR or when you get it depending on your blood cell counts. People who are age 70 or older and women may be more likely to have their blood cells affected.

- Pneumocystis carinii Pneumonia (PCP). PCP is an infection that people can get when their immune system is weak. TEMODAR decreases white blood cells, which makes your immune system weaker and can increase your risk of getting PCP. All patients taking TEMODAR will be watched carefully by their doctor for this infection, especially patients who take steroids. Tell your doctor if you have any of the following signs and symptoms of PCP infection: shortness of breath and/or fever, chills, dry cough.
- Secondary cancers. Blood problems such as myelodysplastic syndrome and secondary cancers, such as a certain kind of leukemia, can happen in people who take TEMODAR. Your doctor will watch you for this.
- Convulsions. Convulsions may be severe or life-threatening in people who take TEMODAR.

Common side effects with TEMODAR include:

- nausea and vomiting. Your doctor can prescribe medicines that may help reduce these symptoms.
- headache
- feeling tired
- loss of appetite
- hair loss
- constipation
- bruising
- rash
- paralysis on one side of the body
- diarrhea
- weakness
- fever
- dizziness
- coordination problems
- viral infection
- sleep problems
- memory loss
- pain, irritation, itching, warmth, swelling or redness at the site of infusion
- bruising or small red or purple spots under the skin

Tell your doctor about any side effect that bothers you or that does not go away.

These are not all the possible side effects with TEMODAR. For more information, ask your doctor or pharmacist.

Call your doctor for medical advice about side effects. You may report side effects to FDA at 1-800-FDA-1088.

How should I store TEMODAR Capsules?

- Store TEMODAR Capsules at 77°F (controlled room temperature). Storage at 59° to 86°F (15° to 30°C) is permitted occasionally.
- Keep TEMODAR Capsules out of the reach of children and pets.

General information about TEMODAR.

Medicines are sometimes prescribed for purposes other than those listed in a Patient Package Insert. Do not use TEMODAR for a condition for which it was not prescribed. Do not give TEMODAR to other people, even if they have the same symptoms that you have. It may harm them.

This leaflet summarizes the most important information about TEMODAR. If you would like more information, talk with your doctor. You can ask your pharmacist or doctor for information about TEMODAR that is written for health professionals.

For more information, go to www.TEMODAR.com or call 1-800-526-4099.

How are TEMODAR Capsules supplied?

TEMODAR Capsules contain a white capsule body with a color cap and the colors vary based on the dosage strength. The capsules are available in six different strengths.

TEMODAR Capsule Strength | Color
5 mg | Green Cap
20 mg | Yellow Cap
100 mg | Pink Cap
140 mg | Blue Cap
180 mg | Orange Cap
250 mg | White Cap

What are the ingredients in TEMODAR?

TEMODAR Capsules:

Active ingredient: temozolomide.

Inactive ingredients: lactose anhydrous, colloidal silicon dioxide, sodium starch glycolate, tartaric acid, stearic acid.

The body of the capsules are made of gelatin and are opaque white. The cap is also made of gelatin, and the colors vary based on the dosage strength. The capsule body and cap are imprinted with pharmaceutical branding ink, which contains shellac, dehydrated alcohol, isopropyl alcohol, butyl alcohol, propylene glycol, purified water, strong ammonia, potassium hydroxide, and ferric oxide.

TEMODAR 5 mg: The green cap contains gelatin, titanium dioxide, iron oxide yellow, sodium lauryl sulfate, and FD&C Blue #2.

TEMODAR 20 mg: The yellow cap contains gelatin, sodium lauryl sulfate, and iron oxide yellow.

TEMODAR 100 mg: The pink cap contains gelatin, titanium dioxide, sodium lauryl sulfate, and iron oxide red.

TEMODAR 140 mg: The blue cap contains gelatin, sodium lauryl sulfate, and FD&C Blue #2.

TEMODAR 180 mg: The orange cap contains gelatin, iron oxide red, iron oxide yellow, titanium dioxide, and sodium lauryl sulfate.

TEMODAR 250mg: The white cap contains gelatin, titanium dioxide, and sodium lauryl sulfate.

TEMODAR for Injection:

Active ingredient: temozolomide.

Inactive ingredients: mannitol, L-threonine, polysorbate 80, sodium citrate dihydrate, and hydrochloric acid.

Issued: February 2009

TEMODAR Capsules
Manufactured by: Schering Corporation, a subsidiary of {corporate logo}MERCK & CO., INC., Whitehouse Station, NJ 08889, USA

TEMODAR for Injection
Manufactured by: Baxter Oncology GmbH, Halle/Westfalen, Germany
Distributed by: Schering Corporation, a subsidiary of {corporate logo}MERCK & CO., INC., Whitehouse Station, NJ 08889, USA

Copyright©1999, 2008 Schering Corporation, a subsidiary of Merck & Co., Inc. All rights reserved.

U.S. Patent Nos. 5,260,291 and 6,987,108.

Rev. 04/10
31851114T

The trademarks depicted in this piece are owned by their respective companies.

PHARMACIST INFORMATION SHEET

What is TEMODAR? [See Full Prescribing Information, Indications and Usage (1)].

TEMODAR® (temozolomide) is an alkylating drug for the treatment of adult patients with newly diagnosed glioblastoma multiforme and refractory anaplastic astrocytoma.

How is TEMODAR dosed? [See Full Prescribing Information, Recommended Dosing and Dose Modification Guidelines (2.1)].

The daily dose of TEMODAR for a given patient is calculated by the physician, based on the patient's body surface area (BSA) [see Table 5 in the Full Prescribing Information, Recommended Dosing and Dose Modification Guidelines (2.1)]. The recommended dose for TEMODAR as an intravenous infusion over 90 minutes is the same as the dose for the oral capsule formulation. Bioequivalence has been established only when TEMODAR for Injection was given over 90 minutes. The dose for subsequent cycles may be adjusted according to nadir neutrophil and platelet counts in the previous cycle and at the time of initiating the next cycle.

Dosing for Patients with Refractory Anaplastic Astrocytoma [See Full Prescribing Information, Recommended Dosing and Dose Modification Guidelines, Patients with Refractory Anaplastic Astrocytoma (2.1)].

Dosage of TEMODAR must be adjusted according to nadir neutrophil and platelet counts in the previous cycle and neutrophil and platelet counts at the time of initiating the next cycle. The initial dose is 150 mg/m^2 orally once daily for 5 consecutive days per 28-day treatment cycle. If both the nadir and day of dosing (Day 29, Day 1 of next cycle) absolute neutrophil counts (ANC) are ≥1.5 × 10^9/L (1500/µL) and both the nadir and Day 29, Day 1 of next cycle platelet counts are ≥100 × 10^9/L (100,000/µL), the TEMODAR dose may be increased to 200 mg/m^2/ day for 5 consecutive days per 28-day treatment cycle. During treatment, a complete blood count should be obtained on Day 22 (21 days after the first dose) or within 48 hours of that day, and weekly until the ANC is above 1.5 × 10^9/L (1500/µL) and the platelet count exceeds 100 × 10^9/L (100,000/µL). The next cycle of TEMODAR should not be started until the ANC and platelet count exceed these levels. If the ANC falls to <1.0 × 10^9/L (1000/µL) or the platelet count is <50 × 10^9/L (50,000/µL) during any cycle, the next cycle should be reduced by 50 mg/m^2, but not below 100 mg/m^2, the lowest recommended dose [see Table 4 in the Full Prescribing Information, Recommended Dosing and Dose Modification Guidelines (2.1)].

Patients should continue to receive TEMODAR until their physician determines that their disease has progressed, or until unacceptable side effects or toxicities occur. Physicians may alter the treatment regimen for a given patient.

Dosing for Patients with Newly Diagnosed Glioblastoma Multiforme [See Full Prescribing Information, Recommended Dosing and Dose Modification Guidelines, Patients with Newly Diagnosed High Grade Glioma (2.1)].

Concomitant Phase Treatment Schedule

TEMODAR is administered at 75 mg/m^2 daily for 42 days concomitant with focal radiotherapy (60 Gy administered in 30 fractions), followed by maintenance TEMODAR for 6 cycles. No dose reductions are recommended; however, dose interruptions may occur based on patient tolerance. The TEMODAR dose can be continued throughout the 42-day concomitant period up to 49 days if all of the following conditions are met: absolute neutrophil count ≥1.5 × 10^9/L, platelet count ≥100 ×10^9/L, common toxicity criteria (CTC) non-hematological toxicity ≤ Grade 1 (except for alopecia, nausea, and vomiting). During treatment a complete blood count should be obtained weekly. Temozolomide dosing should be interrupted or discontinued during concomitant phase according to the hematological and non-hematological toxicity criteria as noted in Table 1 of the Full Prescribing Information under 2.1 Recommended Dosing and Dose Modification Guidelines. PCP prophylaxis is required during the concomitant administration of TEMODAR and radiotherapy and should be continued in patients who develop lymphocytopenia until recovery from lymphocytopenia (CTC Grade ≤1).

Maintenance Phase Treatment Schedule

Four weeks after completing the TEMODAR + RT phase, TEMODAR is administered for an additional 6 cycles of maintenance treatment. Dosage in Cycle 1 (maintenance) is 150 mg/m^2 once daily for 5 days followed by 23 days without treatment. At the start of Cycle 2, the dose can be escalated to 200 mg/m^2, if the CTC non-hematologic toxicity for Cycle 1 is Grade ≤2 (except for alopecia, nausea, and vomiting), absolute neutrophil count (ANC) is ≥1.5 × 10^9/L, and the platelet count is ≥100 × 10^9/L. If the dose was not escalated at Cycle 2, escalation should not be done in subsequent cycles. The dose remains at 200 mg/m^2 per day for the first 5 days of each subsequent cycle except if toxicity occurs.

During treatment a complete blood count should be obtained on Day 22 (21 days after the first dose) or within 48 hours of that day, and weekly until the ANC is above 1.5 × 10^9/L (1500/µL) and the platelet count exceeds 100 × 10^9/L (100,000/µL). The next cycle of TEMODAR should not be started until the ANC and platelet count exceed these levels. Dose reductions during the next cycle should be based on the lowest blood counts and worst nonhematologic toxicity during the previous cycle. Dose reductions or discontinuations during the maintenance phase should be applied according to Tables 2 and 3 in the Full Prescribing Information under 2.1 Recommended Dosing and Dose Modification Guidelines.

How is TEMODAR for Injection prepared? [See Full Prescribing Information, Preparation and Administration, TEMODAR for Injection (2.2)].

Care should be exercised in the handling and preparation of TEMODAR. Vials should not be opened. If vials are accidentally opened or damaged, rigorous precautions should be taken with the contents to avoid inhalation or contact with the skin or mucous membranes. The use of gloves and safety glasses is recommended to avoid exposure in case of breakage of the vial. Procedures for proper handling and disposal of anticancer drugs should be considered^1–4. Several guidelines on this subject have been published.

1. TEMODAR for Injection vials should be stored refrigerated at 2°–8°C (36°–46°F).
2. Bring the vial to room temperature prior to reconstitution with Sterile Water for Injection.
3. Using aseptic technique, reconstitute each vial with 41 mL Sterile Water for Injection. The resulting solution will contain 2.5 mg/mL temozolomide.
4. Vial should be gently swirled and not shaken. Inspect vials, and any vial containing visible particulate matter should not be used. Do not further dilute the reconstituted solution. Upon reconstitution, store at room temperature for up to 14 hours, including infusion time.
5. Using aseptic technique, withdraw up to 40 mL from each vial to make up the total dose and transfer into an empty 250 mL infusion bag.
6. Attach the pump tubing to the bag, purge the tubing and then cap.

How is TEMODAR for Injection administered? [See Full Prescribing Information, Preparation and Administration, TEMODAR for Injection (2.2)].

TEMODAR for Injection is administered as an intravenous infusion over 90 minutes. Bioequivalence has been established only when TEMODAR for Injection was given over 90 minutes. TEMODAR for Injection should be administered only by intravenous infusion. Flush the lines before and after each TEMODAR infusion.

TEMODAR for Injection may be administered in the same intravenous line with 0.9% Sodium Chloride injection only.

Because no data are available on the compatibility of TEMODAR for Injection with other intravenous substances or additives, other medications should not be infused simultaneously through the same intravenous line.

What should the patient avoid during treatment with TEMODAR? [See Full Prescribing Information, Use in Specific Populations, Pregnancy (8.1) and Nursing Mothers (8.3)].

There are no dietary restrictions for patients taking TEMODAR. TEMODAR may affect testicular function, so male patients should exercise adequate birth control measures. TEMODAR may cause birth defects. Female patients should avoid becoming pregnant while receiving this drug. It is not known whether TEMODAR is excreted into breast milk. Because many drugs are excreted in human milk, and because of the potential for serious adverse reactions in nursing infants and tumorigenicity shown for temozolomide in animal studies, a decision should be made whether to discontinue nursing or to discontinue the drug, taking into account the importance of the drug to the mother from TEMODAR.

What are the side effects of TEMODAR? [See Full Prescribing Information, Adverse Reactions (6)].

Nausea and vomiting are the most common side effects associated with TEMODAR. Noncumulative myelosuppression is the dose-limiting toxicity. Patients should be evaluated periodically by their physician to monitor blood counts.

Other commonly reported side effects reported by patients taking TEMODAR are fatigue, constipation, alopecia, anorexia, headache, and bruising, as well as pain, irritation, itching, warmth, swelling, and redness at the site of infusion.

How is TEMODAR supplied? [See Full Prescribing Information, How Supplied/Storage and Handling (16)].

TEMODAR for Injection is supplied in single-use glass vials containing 100 mg temozolomide. TEMODAR is also available as capsules in 5-mg, 20-mg, 100-mg, 140-mg, 180-mg, and 250-mg strengths.

1. OSHA Technical Manual, TED 1-0.15A, Section VI: Chapter 2. Controlling Occupational Exposure to Hazardous Drugs. OSHA, 1999.
2. American Society of Health-System Pharmacists. ASHP guidelines on handling hazardous drugs. Am J Health-Syst Pharm. 2006; 63:1172–1193.
3. NIOSH Alert: Preventing occupational exposures to antineoplastic and other hazardous drugs in healthcare settings. 2004. U.S. Department of Health and Human Services, Public Health Service, Centers for Disease Control and Prevention, National Institute for Occupational Safety and Health, DHHS (NIOSH) Publication No. 2004-165.[3]
4. Polovich, M., White, J. M., & Kelleher, L.O. (eds.) 2005. Chemotherapy and biotherapy guidelines and recommendations for practice (2nd. ed.) Pittsburgh, PA: Oncology.

TEMODAR for Injection
Manufactured by: Baxter Oncology GmbH, Halle/Westfalen, Germany
Distributed by: Schering Corporation, a subsidiary of {corporate logo}MERCK & CO., INC., Whitehouse Station, NJ 08889, USA

Copyright© 2008 Schering Corporation, a subsidiary of Merck & Co., Inc. All rights reserved.

U.S. Patent Nos. 5,260,291, 6,987,108, and 7,786,118.

Rev. 2/11
30984447T

PHARMACIST:

Tear at perforation and give to patient.

PHARMACIST INFORMATION SHEET

BOXED WARNING

IMPORTANT DISPENSING INFORMATION

For every patient, TEMODAR must be dispensed in a separate vial or in its original glass bottle making sure each container lists the strength per capsule and that patients take the appropriate number of capsules from each bottle or vial.

Please see the dispensing instructions below for more information.

What is TEMODAR?

TEMODAR® (temozolomide) is an oral alkylating agent for the treatment of newly diagnosed glioblastoma multiforme and refractory anaplastic astrocytoma.

How is TEMODAR dosed?

The daily dose of TEMODAR Capsules for a given patient is calculated by the physician, based on the patient's body surface area (BSA). The resulting dose is then rounded off to the nearest 5 mg. An example of the dosing may be as follows: the initial daily dose of TEMODAR in milligrams is the BSA multiplied by mg/m^2/day, (a patient with a BSA of 1.84 is 1.84 × 75 mg = 138, or 140 mg/day). The dose for subsequent cycles may be adjusted according to nadir neutrophil and platelet counts in the previous cycle and at the time of initiating the next cycle.

How might the dose of TEMODAR be modified for Refractory Anaplastic Astrocytoma?

Dosage of TEMODAR must be adjusted according to nadir neutrophil and platelet counts in the previous cycle and neutrophil and platelet counts at the time of initiating the next cycle. The initial dose is 150 mg/m^2 orally once daily for 5 consecutive days per 28-day treatment cycle. If both the nadir and day of dosing (Day 29, Day 1 of next cycle) absolute neutrophil counts (ANC) are ≥1.5 × 10^9/L (1500/µL) and both the nadir and Day 29, Day 1 of next cycle platelet counts are ≥100 × 10^9/L (100,000/µL), the TEMODAR dose may be increased to 200 mg/m^2/ day for 5 consecutive days per 28-day treatment cycle. During treatment, a complete blood count should be obtained on Day 22 (21 days after the first dose) or within 48 hours of that day, and weekly until the ANC is above 1.5 × 10^9/L (1500/µL) and the platelet count exceeds 100 × 10^9/L (100,000/µL). The next cycle of TEMODAR should not be started until the ANC and platelet count exceed these levels. If the ANC falls to <1.0 × 10^9/L (1000/µL) or the platelet count is <50 × 10^9/L (50,000/µL) during any cycle, the next cycle should be reduced by 50 mg/m^2, but not below 100 mg/m^2, the lowest recommended dose (see Table 1 below).

TABLE 1: Dosing Modification Table for Refractory Anaplastic Astrocytoma

What is the TEMODAR Capsules treatment regimen?

TEMODAR is given for 5 consecutive days on a 28-day cycle. Patients should continue taking TEMODAR until their physician determines that their disease has progressed, up to 2 years, or until unacceptable side effects or toxicities occur. Physicians may alter the treatment regimen for a given patient.

Newly Diagnosed Concomitant Phase Treatment Schedule

TEMODAR is administered orally at 75 mg/m^2 daily for 42 days concomitant with focal radiotherapy (60Gy administered in 30 fractions), followed by maintenance TEMODAR for 6 cycles. No dose reductions are recommended; however, dose interruptions may occur based on patient tolerance. The TEMODAR dose can be continued throughout the 42-day concomitant period up to 49 days if all of the following conditions are met: absolute neutrophil count ≥1.5 × 10^9/L, platelet count ≥100 ×10^9/L, common toxicity criteria (CTC) nonhematological toxicity ≤Grade 1 (except for alopecia, nausea and vomiting). During treatment a complete blood count should be obtained weekly. Temozolomide dosing should be interrupted or discontinued during concomitant phase according to the hematological and nonhematological toxicity criteria as noted in Table 2. PCP prophylaxis is required during the concomitant administration of TEMODAR and radiotherapy and should be continued in patients who develop lymphocytopenia until recovery from lymphocytopenia (CTC grade ≤1).

TABLE 2: Temozolomide Dosing Interruption or Discontinuation During Concomitant Radiotherapy and Temozolomide
Toxicity | TMZ Interruption [Treatment with concomitant TMZ could be continued when all of the following conditions were met: absolute neutrophil count ≥1.5 × 10^9/L; platelet count ≥100 × 10^9/L; CTC non-hematological toxicity ≤Grade 1 (except for alopecia, nausea, vomiting).] | TMZ Discontinuation
Absolute Neutrophil Count | ≥0.5 and <1.5 × 10^9/L | <0.5 × 10^9/L
Platelet Count | ≥10 and <100 × 10^9/L | <10 × 10^9/L
CTC Nonhematological Toxicity (except for alopecia, nausea, vomiting) | CTC Grade 2 | CTC Grade 3 or 4
TMZ = temozolomide; CTC = Common Toxicity Criteria.

Maintenance Phase Treatment Schedule

Four weeks after completing the TEMODAR + RT phase, TEMODAR is administered for an additional 6 cycles of maintenance treatment. Dosage in Cycle 1 (maintenance) is 150 mg/m^2 once daily for 5 days followed by 23 days without treatment. At the start of Cycle 2, the dose is escalated to 200 mg/m^2 , if the CTC nonhematologic toxicity for Cycle 1 is Grade ≤2 (except for alopecia, nausea and vomiting), absolute neutrophil count (ANC) is ≥1.5 × 10^9/L, and the platelet count is ≥100 × 10^9/L. If the dose was not escalated at Cycle 2, escalation should not be done in subsequent cycles. The dose remains at 200 mg/m^2 per day for the first 5 days of each subsequent cycle except if toxicity occurs.

During treatment a complete blood count should be obtained on Day 22 (21 days after the first dose) or within 48 hours of that day, and weekly until the ANC is above 1.5 × 10^9/L (1500/µL) and the platelet count exceeds 100 × 10^9/L (100,000/µL). The next cycle of TEMODAR should not be started until the ANC and platelet count exceed these levels. Dose reductions during the next cycle should be based on the lowest blood counts and worst nonhematologic toxicity during the previous cycle. Dose reductions or discontinuations during the maintenance phase should be applied according to Tables 3 and 4.

TABLE 3: Temozolomide Dose Levels for Maintenance Treatment
Dose Level | Dose (mg/m^2/day) | Remarks
−1 | 100 | Reduction for prior toxicity
0 | 150 | Dose during Cycle 1
1 | 200 | Dose during Cycles 2–6 in absence of toxicity

TABLE 4: Temozolomide Dose Reduction or Discontinuation During Maintenance Treatment
Toxicity | Reduce TMZ by 1 Dose Level [TMZ dose levels are listed in Table 3.] | Discontinue TMZ
Absolute Neutrophil Count | <1.0 × 10^9/L | See footnote [TMZ is to be discontinued if dose reduction to <100 mg/m^2 is required or if the same Grade 3 nonhematological toxicity (except for alopecia, nausea, vomiting) recurs after dose reduction.]
Platelet Count | <50 × 10^9/L | See footnote
CTC Nonhematological Toxicity (except for alopecia, nausea, vomiting) | CTC Grade 3 | CTC Grade 4
TMZ = temozolomide; CTC = Common Toxicity Criteria.

How is TEMODAR taken?

Patients should take each day's dose with a full glass of water at the same time each day. Taking the medication on an empty stomach or at bedtime may help ease nausea. If patients are also taking antinausea or other medications to relieve the side effects associated with TEMODAR, they should be advised to take these medications 30 minutes before they take TEMODAR. Temozolomide causes the rapid appearance of malignant tumors in rats. Patients SHOULD NOT open or split the capsules. If capsules are accidentally opened or damaged, rigorous precautions should be taken with the capsule contents to avoid inhalation or contact with the skin or mucous membranes. The medication should be kept away from children and pets. The TEMODAR capsules should be swallowed whole and NEVER CHEWED.

What should the patient avoid during treatment with TEMODAR?

There are no dietary restrictions for patients taking TEMODAR. TEMODAR may affect testicular function, so male patients should exercise adequate birth control measures. TEMODAR may cause birth defects. Female patients should avoid becoming pregnant while receiving this drug. Women who are nursing prior to receiving TEMODAR should discontinue nursing. It is not known whether TEMODAR is excreted into breast milk.

What are the side effects of TEMODAR?

Nausea and vomiting are the most common side effects associated with TEMODAR. Noncumulative myelosuppression is the dose-limiting toxicity. Patients should be evaluated periodically by their physician to monitor blood counts.

Other commonly reported side effects reported by patients taking TEMODAR are fatigue, constipation, alopecia, anorexia, and headache.

How is TEMODAR supplied?

TEMODAR Capsules are available in 5-mg, 20-mg, 100-mg, 140-mg, 180-mg, and 250-mg strengths. The capsules contain a white capsule body with a color cap, and the colors vary based on the dosage strength.

TEMODAR Capsule Strength | Color
5 mg | Green Cap
20 mg | Yellow Cap
100 mg | Pink Cap
140 mg | Blue Cap
180 mg | Orange Cap
250 mg | White Cap

The 5-mg, 20-mg, 100-mg, 140-mg, and 180-mg capsule strengths are available in 5-count and 14-count packages. The 250-mg capsule strength is available in a 5-count package.

How is TEMODAR dispensed?

Each strength of TEMODAR must be dispensed in a separate vial or in its original glass bottle (one strength per one container). Follow the instructions below:

Based on the dose prescribed, determine the number of each strength of TEMODAR capsules needed for the full 42- or 5-day cycle as prescribed by the physician. For example, in a 5-day cycle, 275 mg/day would be dispensed as five 250-mg capsules, five 20-mg capsules and five 5-mg capsules. Label each container with the appropriate number of capsules to be taken each day. Dispense to the patient, making sure each container lists the strength (mg) per capsule and that he or she understands to take the appropriate number of capsules of TEMODAR from each bottle or vial to equal the total daily dose prescribed by the physician.

How can TEMODAR be ordered?

TEMODAR can be ordered from your wholesaler. It is important to understand if TEMODAR is being used as part of a 42-day regimen or as part of a 5-day course. Remember to order enough TEMODAR for the appropriate cycle.

For example:

- a 5-day course of 360 mg/day would require the following to be ordered: two 5-count packages of 180-mg capsules.
- a 42-day course of 140 mg/day would require the following to be ordered: three 14-count packages of 140-mg capsules.

For examples of other dosing regimens, please refer to the full Prescribing Information (Table 10)

TEMODAR Product | NDC Number
5-mg capsules (5 count) | 0085-3004-02
5-mg capsules (14 count) | 0085-3004-01
20-mg capsules (5 count) | 0085-1519-02
20-mg capsules (14 count) | 0085-1519-01
100-mg capsules (5 count) | 0085-1366-02
100-mg capsules (14 count) | 0085-1366-01
140-mg capsules (5 count) | 0085-1425-01
140-mg capsules (14 count) | 0085-1425-02
180-mg capsules (5 count) | 0085-1430-01
180-mg capsules (14 count) | 0085-1430-02
250-mg capsules (5 count) | 0085-1417-01

Manufactured by: Schering Corporation, a subsidiary of {corporate logo}MERCK& CO., INC., Whitehouse Station, NJ 08889 USA

Copyright© 2005 Schering Corporation, a subsidiary of Merck & Co., Inc. All rights reserved.
U.S. Patent No. 5,260,291.
33276915T
Rev. 4/10

PACKAGE LABEL

PRINCIPAL DISPLAY PANEL - 5 mg Capsule

5 mg
per capsule

Temodar®
(temozolomide)
Capsules

For Oral Administration
Rx only

PACKAGE LABEL

PRINCIPAL DISPLAY PANEL - 20 mg Capsule

20 mg
per capsule

Temodar®
(temozolomide)
Capsules

For Oral Administration
Rx only

PACKAGE LABEL

PRINCIPAL DISPLAY PANEL - 100 mg Capsule

100 mg
per capsule

Temodar®
(temozolomide)
Capsules

For Oral Administration
Rx only

PACKAGE LABEL

PRINCIPAL DISPLAY PANEL - 180 mg Capsule

180 mg
per capsule

Temodar®
(temozolomide)
Capsules

For Oral Administration
Rx only

PACKAGE LABEL

PRINCIPAL DISPLAY PANEL - 250 mg Capsule

250 mg
per capsule

Temodar®
(temozolomide)
Capsules

For Oral Administration
Rx only